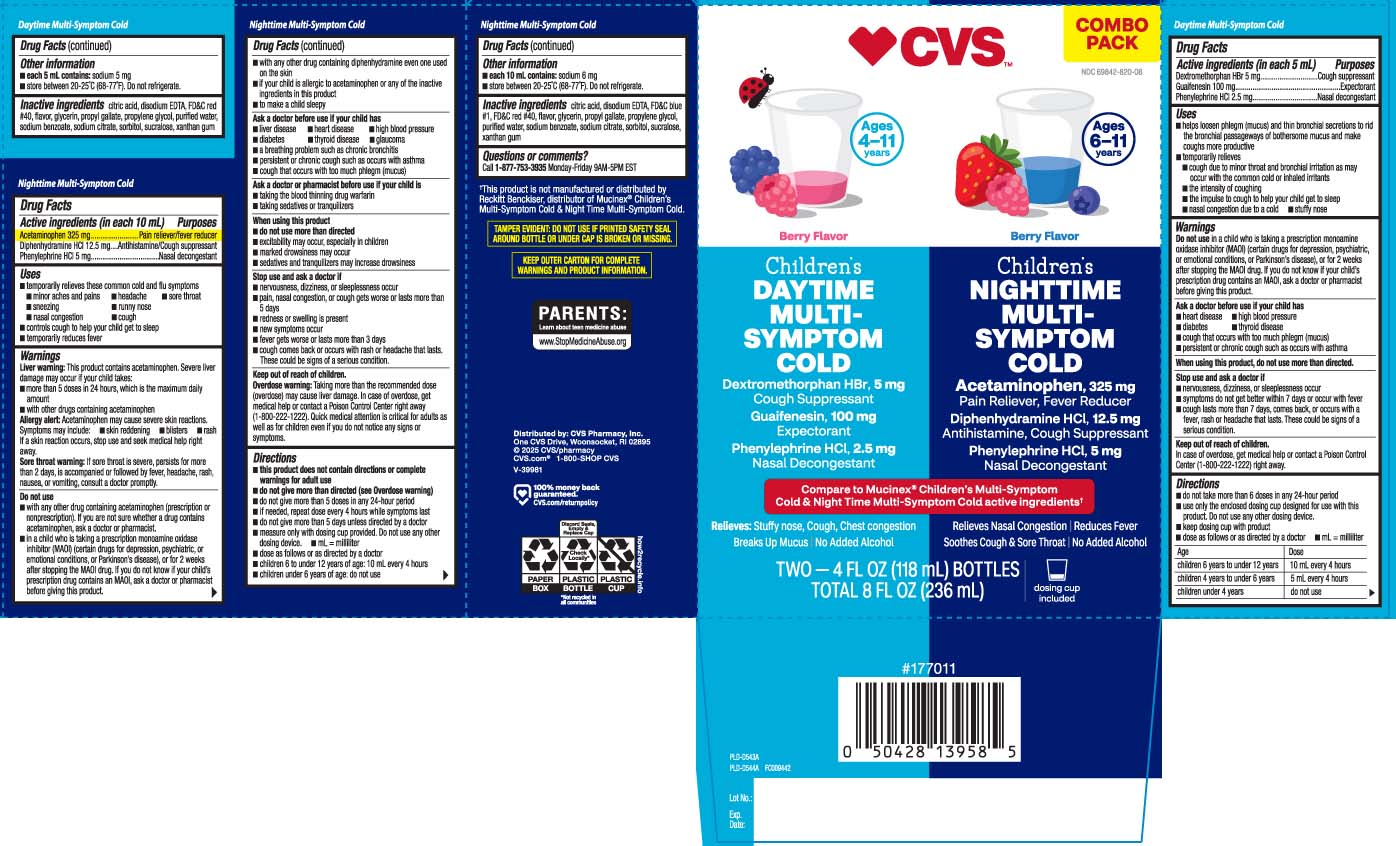 DRUG LABEL: Multi Symptom Cold and Multi Symptom Nighttime Cold
NDC: 69842-820 | Form: KIT | Route: ORAL
Manufacturer: CVS Pharmacy
Category: otc | Type: HUMAN OTC DRUG LABEL
Date: 20250912

ACTIVE INGREDIENTS: DEXTROMETHORPHAN HYDROBROMIDE 5 mg/5 mL; GUAIFENESIN 100 mg/5 mL; PHENYLEPHRINE HYDROCHLORIDE 2.5 mg/5 mL; ACETAMINOPHEN 325 mg/10 mL; DIPHENHYDRAMINE HYDROCHLORIDE 12.5 mg/10 mL; PHENYLEPHRINE HYDROCHLORIDE 5 mg/10 mL
INACTIVE INGREDIENTS: ANHYDROUS CITRIC ACID; EDETATE CALCIUM DISODIUM; FD&C RED NO. 40; GLYCERIN; PROPYL GALLATE; PROPYLENE GLYCOL; WATER; SODIUM BENZOATE; SODIUM CITRATE; SORBITOL; SUCRALOSE; XANTHAN GUM; ANHYDROUS CITRIC ACID; EDETATE CALCIUM DISODIUM; FD&C BLUE NO. 1; FD&C RED NO. 40; GLYCERIN; PROPYL GALLATE; PROPYLENE GLYCOL; WATER; SODIUM BENZOATE; SODIUM CITRATE; SORBITOL; SUCRALOSE; XANTHAN GUM

DRUG FACTS

Active ingredients for Nighttime (in each 10 mL)

Acetaminophen 325 mg

Diphenhydramine HCI 12.5 mg

Phenylephrine HCI 5 mg

Active ingredients for Daytime (in each 5 mL)

Dextromethorphan HBr 5 mg

Guaifenesin 100 mg

Phenylephrine HCl 2.5 mg

Purpose for Nighttime

Pain reliever / fever reducer

Antihistamine / Cough suppressant

Nasal Decongestant

Purpose for Daytime

Cough suppressant

Expectorant

Nasal decongestant

Uses

Nighttime

- temporarily relieves these common cold and flu symptoms

- minor aches and pains
- headache
- sore throat
- sneezing
- runny nose
- nasal congestion
- cough

- controls cough to help your child get to sleep
- temporarily reduces fever

Daytime

- helps loosen phlegm (mucus) and thin bronchial secretions to rid the bronchial passageways of bothersome mucus and make cough more productive
- temporarialy relieves
  - cough due to minor throat and bronchial irritation as may occur with the common cold or inhaled irritants
  - the intensity of coughing
  - the impulse to cough to help your child get to sleep
  - nasal congestion due to a cold
  - stuffy nose

Warnings

NIGHTTIME

Liver warning: This product contains acetaminophen. Severe liver damage may occur if your child takes:

- more than 5 doses in 24 hours, which is the maximum daily amount
- with other drugs containing acetaminophen

Allergy alert: Acetaminophen may cause severe skin reactions. Symptoms may include:

- skin reddening
- blisters
- rash

If a skin reaction occurs, stop use and seek medical help right away.

Sore throat warning: If sore throat is severe, persists for more than 2 days, is accompanied or followed by fever, headache, rash, nausea,or vomiting, consult a doctor promptly.

Do not use

Nighttime

- with any other drug containing acetaminophen (prescription or nonprescription). If you are not sure whether a drug contains acetaminophen, ask a doctor or pharmacist
- in a child who is taking prescription monoamine oxidase inhibitor (MAOI) (certain drugs for depression, psychiatric or emotional conditions, or Parkinson’s disease), or for 2 weeks after stopping the MAOI drug. If you do not know if your child's prescription drug contains an MAOI, ask a doctor or pharmacist before giving this product
- with any other drug containing diphenhydramine, even one used on skin.
- If your child is allergic to acetaminophen or any of the inactive ingredients in this product
- to make a child sleepy

Daytime

- in a child who is taking a prescription monoamine oxidase inhibitor (MAOI)(certain drugs for depression,psychiatic or emotional conditions, or Parkinson's disease), or for 2 weeks after stopping the MAOI drug. If you do not know if your prescription drug contains an MAOI, ask a doctor or pharmacist before giving this product.

Ask a doctor before use if you have

Nighttime

- liver disease
- heart disease
- thyroid disease
- diabetes
- glaucoma
- high blood pressure
- a breathing problem such as chronic bronchitis
- persistent or chronic cough such as occurs with asthma
- cough that occurs with too much phlegm (mucus)

Daytime

- heart disease
- high blood pressure
- thyroid disease
- diabetes
- cough that occurs with too much phlegm (mucus)
- persistent or chronic cough such as occurs with asthma

Ask a doctor or pharmacist before use if you are

Nighttime

- taking the blood thinning drug warfain
- taking sedative or tranquilizers

When using these products

Nighttime

- do not use more than directed
- marked drowsiness may occur
- excitablity may occur, especially in children
- sedatives and tranquilizer may increase drowsiness

Daytime

- do not use more than directed

Stop use and ask a doctor if

Nighttime

- nervousness, dizziness, or sleeplessness occur
- pain, nasal congestion, or cough gets worse or last more than 5 days
- redness or swelling is present
- new symptoms occurs
- fever gets worse or lasts more than 3 days
- cough comes back or occurs with rash or headache that lasts. These could be signs of a serious conditions.

Daytime

- nervousness, dizziness or sleeplessness occur
- symptoms do not better within 7 days or occur with fever
- cough lasts more than 7 days, comes back or occur with a fever, rash, or headache that lasts. These could be signs of a serious condition.

Keep out of reach of children.

Nighttime

Overdose warning: Taking more than the recommended dose (overdose) may cause liver damage.In case of overdose, get medical help or contact a Poison Control Center right away (1-800-222-1222). Quick medical attention is critical even if you do not notice any sign or symptoms.

Daytime

In case of overdose, get medical help or contact a Poison Control Center (1-800-222-1222) right away.

Directions

Nighttime

- this product does not contain directions or complete warnings for adult use
- do not give more than directed (see Overdose warning)
- do not give more than 5 doses in any 24-hour period
- if needed, repeat dose every 4 hours while symptoms last
- do not give more than 5 days unless directed by a doctor
- measure only with dosing cup provided. Do not use any other dosing device.
- mL = milliliter
- dose as follows or as directed by a doctor
- children 6 to under 12 years of age: 10 mL every 4 hours
- children under 6 years of age: do not use

Daytime

- do not take more than 6 doses in any 24-hours period
- use only the enclosed dosing cup designed for use with this product. Do not use any other dosing device
- keep dosing cup with product
- dose as follows, or as directed by a doctor
- mL = milliliter

Age | Dose
children 6 years to under 12 years | 10 mL every 4 hours
children 4 years to under 6 years | 5 mL every 4 hours
children under 4 years | do not use

Other information

Nighttime

- each 10 mL contains: sodium 6 mg
- store between 20-25ºC (68-77ºF). Do not refrigerate.

Daytime

- each 5 mL contains: 5 mg
- store between 20-25ºC (68-77ºF). Do not refrigerate.

Inactive ingredients

Nighttime

citric acid, disodium EDTA, FD&C Blue #1, FD&C red #40, Flavor, glycerin, propyl gallate, propylene glycol, purified water, sodium benzoate, sodium citrate, sorbitol, sucralose, xanthan gum

Daytime

citric acid, disodium EDTA, FD&C red #40, flavor, glycerin, propyl gallate, propylene glycol, purified water, sodium benzoate, sodium citrate, sorbitol, sucralose xanthan gum

Questions or comments?

Call 1-877-753-3935 Monday-Friday 9AM-5PM EST

Principal Display Panel

Compare to Mucinex® Children's Multi-Symptom Cold & Night Time Multi-Symptom Cold active ingredient†

Children's

NIGHTTIME MULTI-SYMPTOM COLD

Acetaminophen 325 mg Pain Reliever, Fever Reducer

Diphenhydramine HCI 12.5 mg Antihistamine,Cough Suppressant

Phenhydramine HCI 5 mg Nasal Decongestant

Relieves:

Nasal and chest congestion

Reduces Fever

Soothes Cough and Sore Throat

No Added Alcohol

Berry Flavor

Ages 6-11 years

Dosage Cup Included

Ages 6 - 11 Years

FL OZ (mL)

TAMPER EVIDENT: DO NOT USE IF PRINTED SAFETY SEAL AROUND BOTTLE OR UNDER CAP IS BROKEN OR MISSING.

KEEP OUTER CARTON FOR COMPLETE WARNINGS AND PRODUCT INFORMATION

†This product is not manufactured or distributed by Reckitt Benckiser, distributor of Mucinex® Children's Multi-Symptom Cold & Night Time Multi-Symptom Cold.

DAYTIME

Children's

DAYTIME MULTI-SYMPTOM COLD

Dextromethorphan HBr 5 mg Cough Suppressant

Guaifenesin 100 mg Expectorant

Phenylephrine HCI 2.5 mg Nasal Decongestant

Relieves: Stuffy nose, Cough, Chest congestion

Breaks up Mucus

No Added Alcohol

Berry Flavor

Dosage cup included

Ages 4 to 11 years

FL OZ (mL)

Distributed by: CVS Pharmacy, Inc.

One CVS Drive, Woonsocket, RI 02895

1-800-SHOP CVS

Product Label

CVS Children's Daytime Multi-Symptom Cold Nighttime Multi-Symptom Cold Berry Flavor